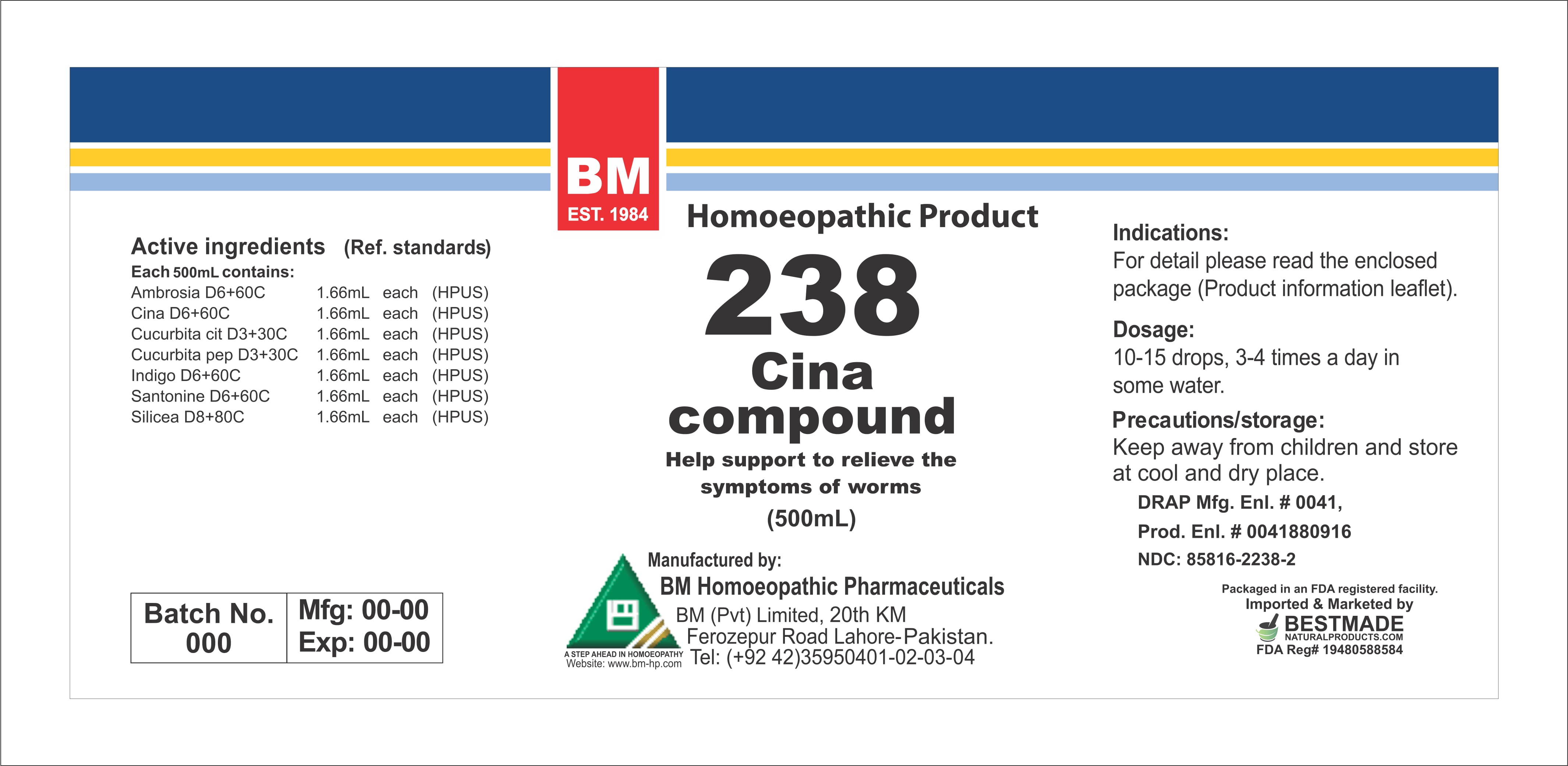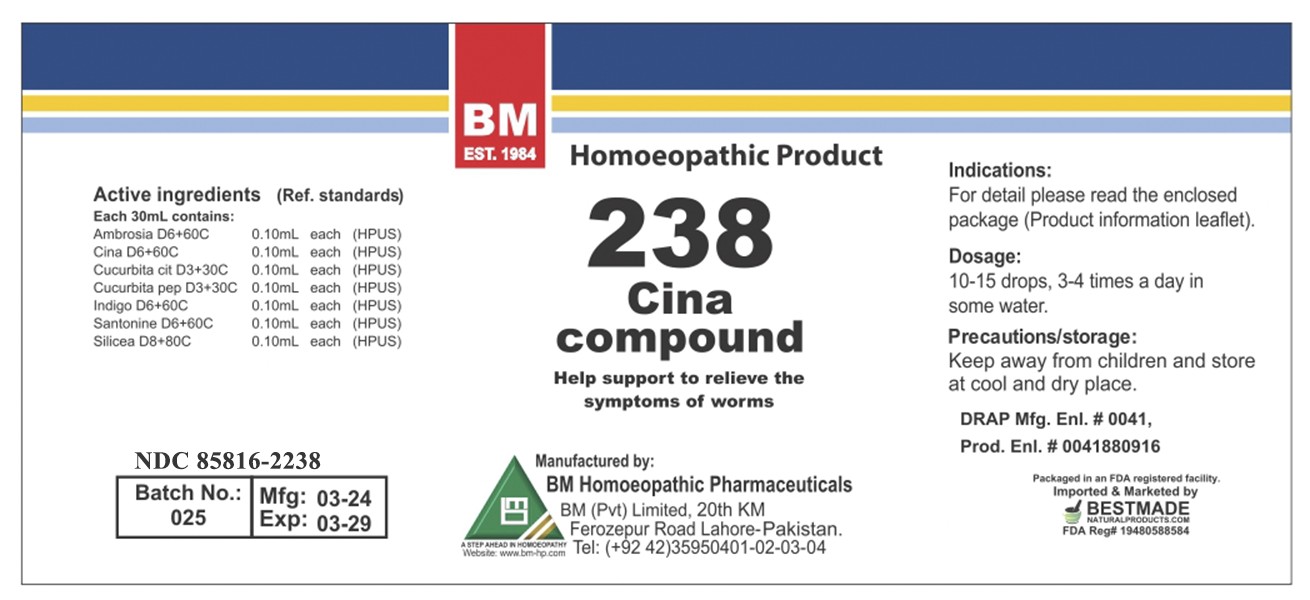 DRUG LABEL: CINA
NDC: 85816-2238 | Form: LIQUID
Manufacturer: BM PRIVATE LIMITED
Category: homeopathic | Type: HUMAN OTC DRUG LABEL
Date: 20260215

ACTIVE INGREDIENTS: INDIGO 6 [hp_X]/1 mL; SILICON DIOXIDE 8 [hp_X]/1 mL; CUCURBITA PEPO FLOWER 3 [hp_X]/1 mL; SANTONIN 6 [hp_X]/1 mL; ARTEMISIA CINA FLOWER 6 [hp_X]/1 mL; WATERMELON SEED 3 [hp_X]/1 mL; AMBROSIA ARTEMISIIFOLIA 6 [hp_X]/1 mL
INACTIVE INGREDIENTS: ALCOHOL 0.96 mL/1 mL

BM HOMEOPATHIC LIQUID CINA / BM238

DOSAGE AND ADMINISTRATION

10-15 drops, 3-4 times a day in some water

ACTIVE INGREDIENT

ambrosia, cina, cucurbita cit, cucurbita pep, indigo, santonine, silicea

INACTIVE INGREDIENT

ALCOHOL

INDICATIONS AND USAGE

For detail, please read the enclosed package (product information leaflet)

PURPOSE

For detail, please read the enclosed package (product information leaflet)

WARNINGS

Precautions/storage:
Keep away from children and store at cool and dry place.

KEEP OUT OF REACH OF CHILDREN

Precautions/storage:
Keep away from children and store at cool and dry place.

PACKAGE LABEL

Pakage 1:

Package 2: